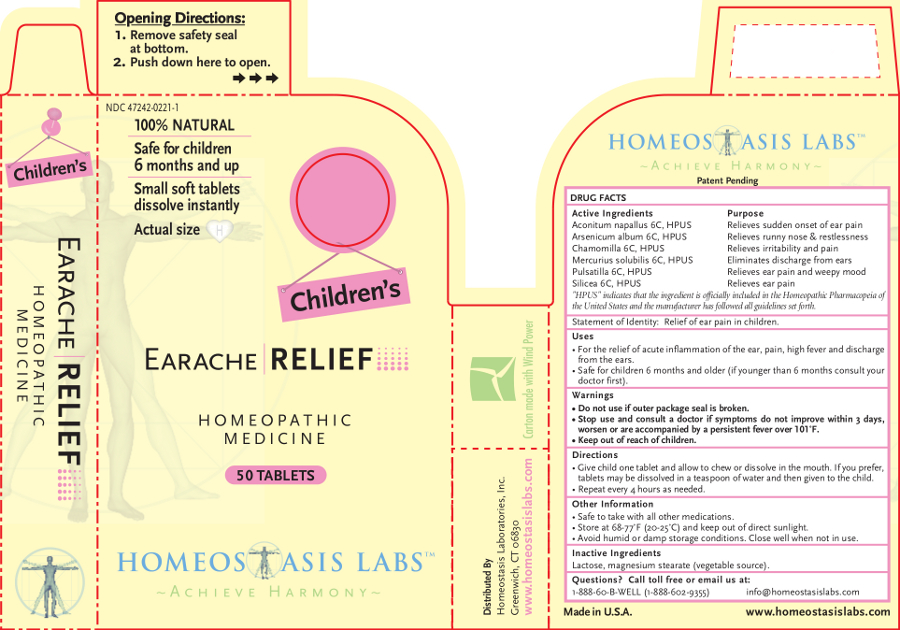 DRUG LABEL: Childrens Earache RELIEF
NDC: 47242-0221 | Form: TABLET, CHEWABLE
Manufacturer: Homeostasis Laboratories, Inc.
Category: homeopathic | Type: HUMAN OTC DRUG LABEL
Date: 20121114

ACTIVE INGREDIENTS: ARSENIC TRIOXIDE 6 [hp_C]/1 1; MATRICARIA RECUTITA 6 [hp_C]/1 1; ACONITUM NAPELLUS 6 [hp_C]/1 1; PULSATILLA VULGARIS 6 [hp_C]/1 1; MERCURIUS SOLUBILIS 6 [hp_C]/1 1; SILICON DIOXIDE 6 [hp_C]/1 1
INACTIVE INGREDIENTS: LACTOSE; MAGNESIUM STEARATE

Children's Earache RELIEF

Active Ingredients | Purpose
Aconitum napallus 6C, HPUS | Relieves sudden onset of ear pain
Arsenicum album 6C, HPUS | Relieves runny nose & restlessness
Chamomilla 6C, HPUS | Relieves irritability and pain
Mercurius solubilis 6C, HPUS | Eliminates discharge from ears
Pulsatilla 6C, HPUS | Relieves ear pain and weepy mood
Silicea 6C, HPUS | Relieves ear pain

"HPUS" indicates that the ingredient is officially included in the Homeopathic Pharmacopeia of the United States and the manufacturer has followed all guidelines set forth.

Statement of Identity: Relief of ear pain in children.

Uses

For the relief of acute inflammation of the ear, pain, high fever and discharge from the ears.

Safe for children 6 months and older (if younger than 6 months consult your doctor first).

Warnings

- Do not use if outer package seal is broken.
- Stop use and consult a doctor if symptoms do not improve within 3 days, worsen or are accompanied by a persistent fever over 101˚F.

- Keep out of reach of children.

Directions

Give child one tablet and allow to chew or dissolve in the mouth. If you prefer, tablets may be dissolved in a teaspoon of water and then given to the child.

Repeat every 4 hours as needed.

Other information

- Safe to take with all other medications.
- Store at 68-77°F (20-25°C) and keep out of direct sunlight.
- Avoid humid or damp storage conditions. Close well when not in use.

Inactive Ingredients

Lactose, magnesium stearate (vegetable source).

Questions? Call toll free or email us at:

1-888-60-B-WELL (1-888-602-9355)

info@homeostasislabs.com